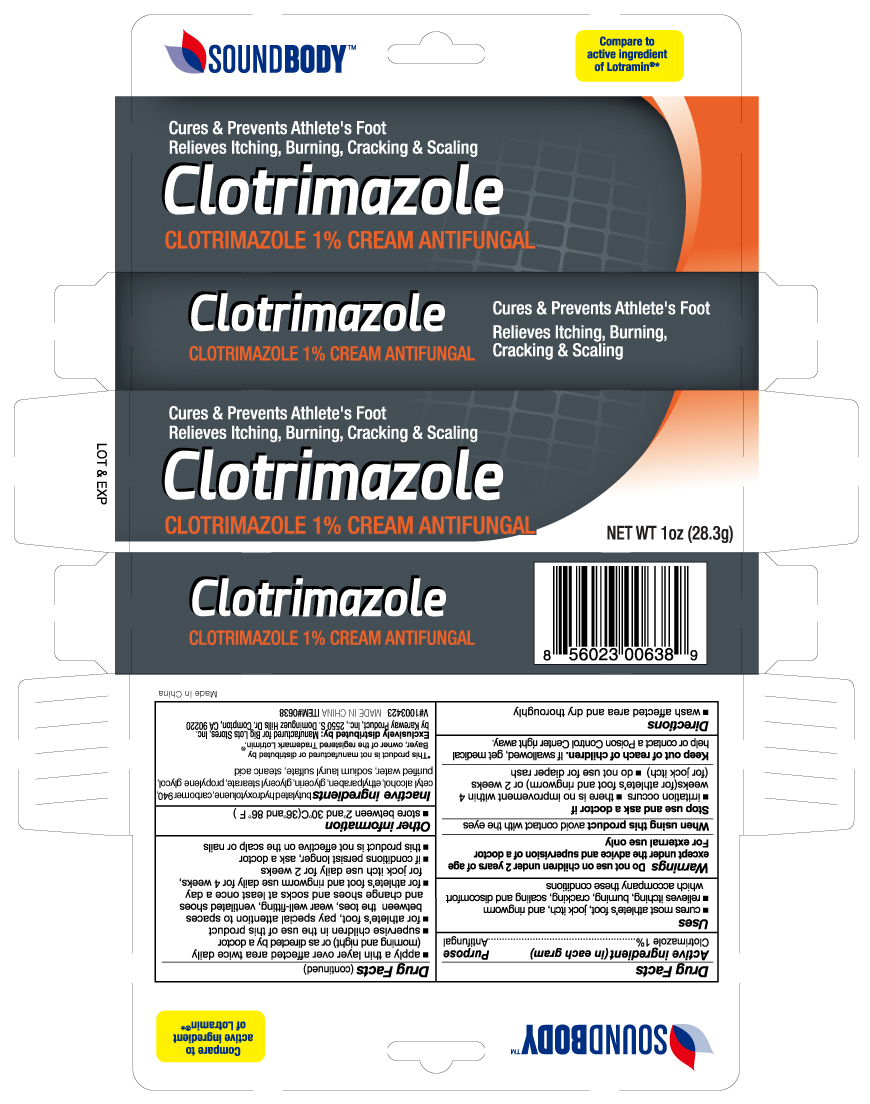 DRUG LABEL: Clotrimazole
NDC: 67510-0638 | Form: CREAM
Manufacturer: Kareway Product, Inc.
Category: otc | Type: HUMAN OTC DRUG LABEL
Date: 20230217

ACTIVE INGREDIENTS: CLOTRIMAZOLE 1 g/100 g
INACTIVE INGREDIENTS: SODIUM LAURYL SULFATE; GLYCERYL 1-STEARATE; CARBOMER 940; CETYL ALCOHOL; GLYCERIN; PROPYLENE GLYCOL; ETHYLPARABEN; STEARIC ACID; BUTYLATED HYDROXYTOLUENE; WATER

Soundbody Clotrimazole

Active Ingredient

Clotrimazole 1%

Purpose

Antifungal

Uses

- cures most athlete's foot, jock itch, and ringworm
- relieves itching, burning, cracking, scaling and discomfort which accompany these conditions

Warnings

Do not use on children under 2 years of age except under the advice and supervision of a doctor

For external use only

When using this product

avoid contact with the eyes

Stop use and ask a doctor if

- irritation occurs
- there is no improvement within 4 weeks(for athlete's foot and ringworm) or 2 weeks (for jock itch)
- do not use for diaper rash

Keep out of reach of children

If swallowed, get medical help or contact a Poison Control Center right away.

Directions

- wash affected area and dry thoroughly
- apply a thin layer cover affected area twice daily (morning and night) or as directed by a doctor
- supervise children in the use of this product
- for athlete's foot, pay special attention to spaces between the toes, wear well-fitting, ventilated shoes and change shoes and socks at least once a day
- for athlete's foot and ringworm use daily for 4 weeks, for jock itch use daily for 2 weeks
- if conditions persist longer, ask a doctor
- this product is not effective on the scalp or nails

Other information

- store between 2°and 30° C (36° and 86° F)

Inactive ingredients

butylated hydroxytoluene, carbomer 940, cetyl alcohol, ethylparaben, glycerin, glyceryl stearate, propylene glycol, sodium lauryl sulfate, stearic acid, water

PACKAGE LABEL

Clotrimazole